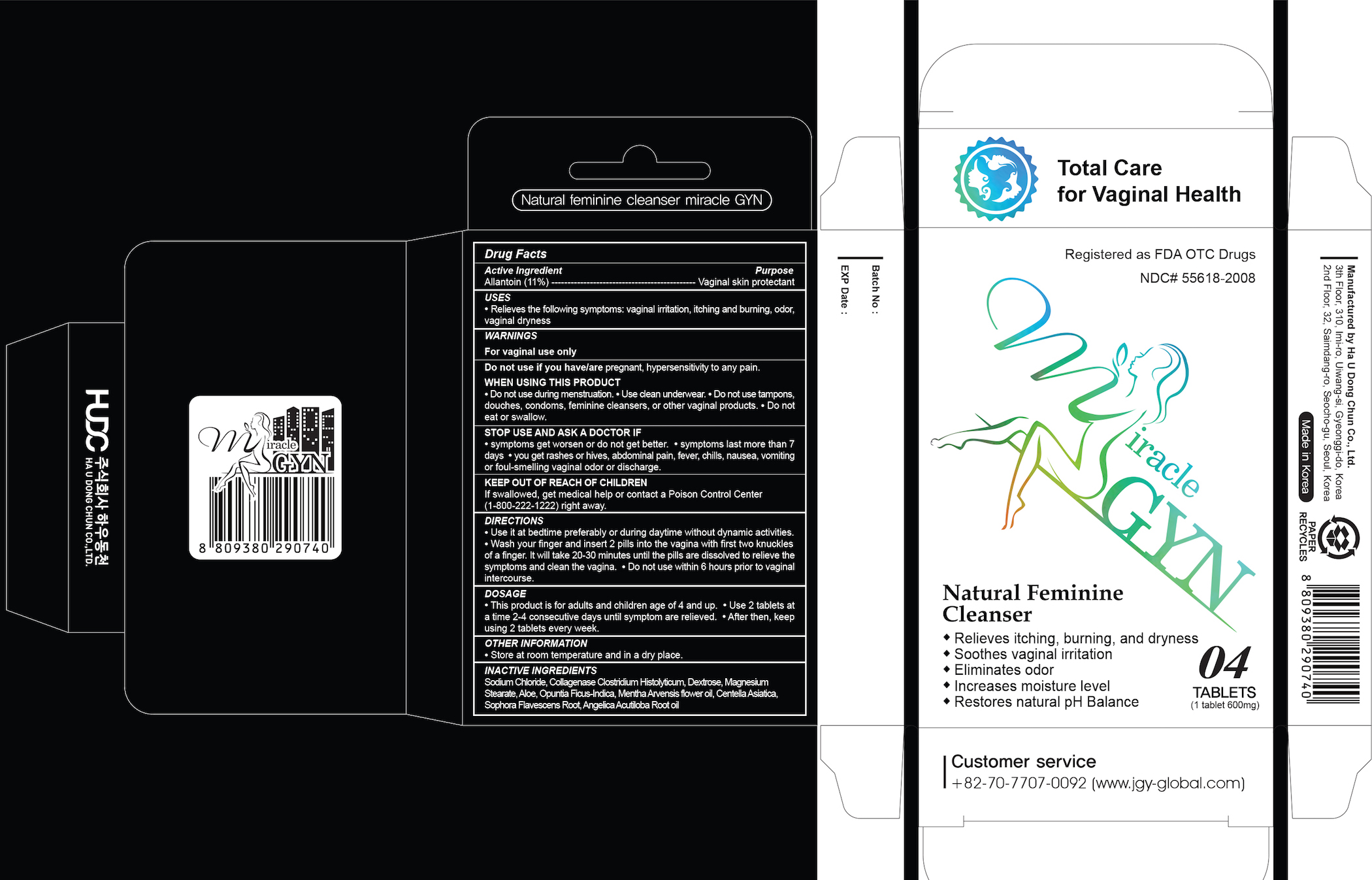 DRUG LABEL: Miracle GYN (4 Tablets)
NDC: 55618-2008 | Form: TABLET
Manufacturer: Haudongchun Co., Ltd.
Category: otc | Type: HUMAN OTC DRUG LABEL
Date: 20170822

ACTIVE INGREDIENTS: ALLANTOIN 66 mg/600 mg
INACTIVE INGREDIENTS: .ALPHA.-D-GLUCOPYRANOSE; MENTHA PIPERITA LEAF; CENTELLA ASIATICA; GINKGO; SOPHORA FLAVESCENS ROOT; ANGELICA GIGAS ROOT; SODIUM CHLORIDE; MAGNESIUM STEARATE; ALOE VERA LEAF

Miracle GYN (4 Tablets)

Active ingredient

Allantoin (11%)

Purpose

Vaginal skin protectant

Keep out of reach of children

If swallowed, get medical help or contact a Poison Control right away. (1-800-222-1222)

Uses

- Relieves the following symptoms: vaginal irritation, itching and burning, odor, vaginal dryness

Warnings

For vaginal use only

Do not use if you have/are pregnat, hypersensitivity to any pain.

When using this product

- do not use during menstruation

- use clean underwear

- do not use tampons, douches, condoms, feminine clenasers, or other vaginal products

- do not eat or swallow

Stop use and ask a doctor if

- symptoms get worsen or do not get better

- symptoms last more than 7days

- you get rashes or hives, abdominal pain, fever, chillis, nausea, vomiting or foul-smelling vaginal odor or discharge

Store at room tmperature and in a dry place.

Directions

- Use it at bedtime preferably or during daytime without dynamic activites.

- Wash your finger and insert 2 pills into the vagina with first two knuckels of a finger. It will take 20-30 minutes until the pills are dissolved to relieve the symptoms and clean the vagina.

- Do not use within 6 hours prior to vaginal intercourse.

Dosage

- This product is for adults and children age of 4 and up.

- Use 2 tablets at a time 2-4 consecutive days until symptom are relieved.

- After then, keep using 2 tablets every week.

Inactive ingredients

Sodium Chloride, Soluble Collagen, Glucose, Magnesium Stearate, Aloe Barbadensis Leaf Extract, Cereus Grandiflorus (Cactus) Extract, Ginkgo Biloba Leaf Extract, Mentha Piperita (Peppermint) Leaf Extract, Centella Asiatica Extract, Sophora Flavescens Root Extract, Angelica Gigas Root Extract